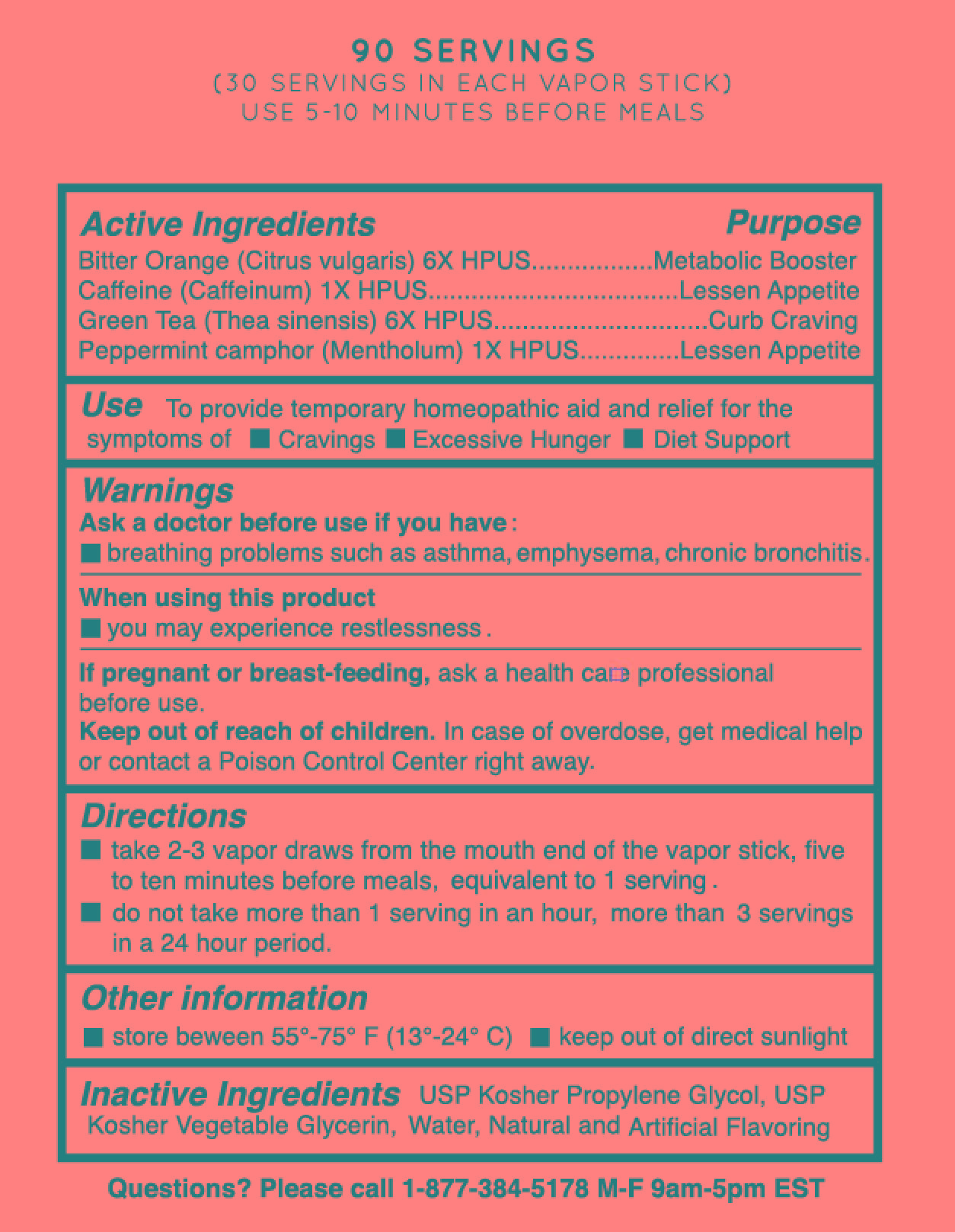 DRUG LABEL: Vapergy Slim
NDC: 69466-002 | Form: SPRAY
Manufacturer: Vapergy USA LLC
Category: homeopathic | Type: HUMAN PRESCRIPTION DRUG LABEL
Date: 20200204

ACTIVE INGREDIENTS: CAFFEINE 1 [hp_X]/1 1; BITTER ORANGE OIL 6 [hp_X]/1 1; GREEN TEA LEAF 6 [hp_X]/1 1; MENTHOL, UNSPECIFIED FORM 1 [hp_X]/1 1
INACTIVE INGREDIENTS: PROPYLENE GLYCOL; GLYCERIN; WATER

Vapergy Slim

Active Ingredients Purpose

Bitter Orange (Citrus Vulgaris) 6X HPUS ............... Metabolic Booster

Caffeine (Caffeinum) 1X HPUS ................................ Lessen Appetite

Green Tea (Thea Sinensis) 6X HPUS ............................ Curb Craving

Peppermint Camphor (Mentholum) 1X HPUS ........... Lessen Appetite

Use

to provide temporary homeopathic aid and relief for the symptoms of

- cravings
- excessive hunger
- diet support

Keep out of reach of children. In case of overdose, get medical help or contact a Poison Control Center right away.

INDICATIONS AND USAGE

Vapergy Vapor Stick

Directions

- take 2-3 vapor draws from the mouth end of the vapor stick, five to ten minutes before meals, equivalent to 1 serving.
- do not take more than 1 serving in an hour, more than 3 servings in a 24 hour period.

Warnings

Ask a doctor before use if you have:

- breathing problems such as asthma, emphysema, chronic bronchitis

When using this product

- you may experience restlessness.

If pregnant or breast-feeding ask a health care professional before use.

Inactive Ingredients

USP Kosher propylene glycol, USP kosher vegetable glycerin, water, natural and artificial flavoring.